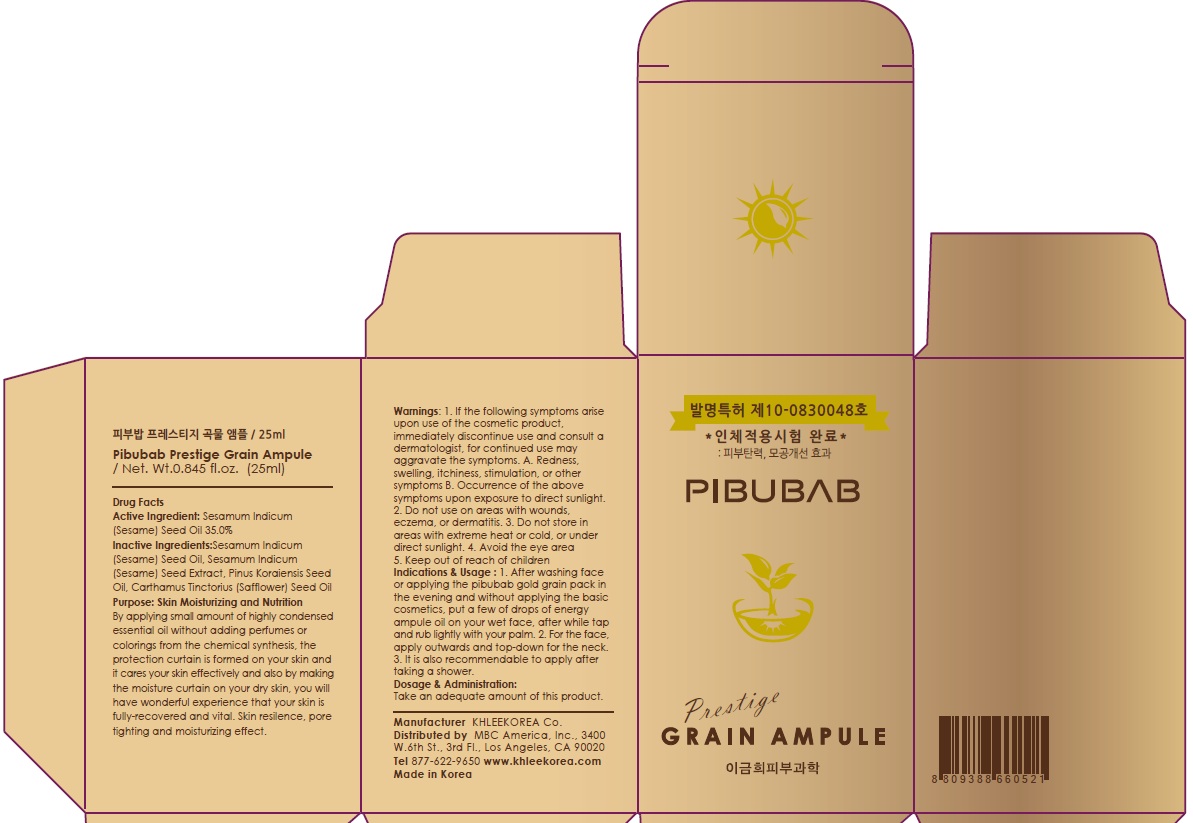 DRUG LABEL: Pibubab Prestige Grain Ampule
NDC: 70567-010 | Form: SOLUTION
Manufacturer: KHLEEKOREA
Category: otc | Type: HUMAN OTC DRUG LABEL
Date: 20160418

ACTIVE INGREDIENTS: SESAME OIL 8.75 g/25 mL
INACTIVE INGREDIENTS: SESAME SEED; PINUS KORAIENSIS SEED OIL

ACTIVE INGREDIENT

Active Ingredient: Sesamum Indicum (Sesame) Seed Oil 35.0%

INACTIVE INGREDIENT

Inactive Ingredients: Sesamum Indicum (Sesame) Seed Extract, Pinus Koraiensis Seed Oil, Carthamus Tinctorius (Safflower) Seed Oil

PURPOSE

Purpose: Skin Moisturizing and Nutrition

By applying small amount of highly condensed essential oil without adding perfumes or colorings from the chemical synthesis, the protection curtain is formed on your skin and it cares your skin effectively and also by making the moisture curtain on your dry skin, you will have wonderful experience that your skin is fully-recovered and vital. Skin resilence, pore tighting and moisturizing effect.

WARNINGS

Warnings: 1. If the following symptoms arise upon use of the cosmetic product, immediately discontinue use and consult a dermatologist, for continued use may aggravate the symptoms. A. Redness, swelling, itchiness, stimulation, or other symptoms B. Occurrence of the above symptoms upon exposure to direct sunlight. 2. Do not use on areas with wounds, eczema, or dermatitis. 3. Do not store in areas with extreme heat or cold, or under direct sunlight. 4. Avoid the eye area 5. Keep out of reach of children

KEEP OUT OF REACH OF CHILDREN

INDICATIONS & USAGE

Indications & Usage: Softly apply cream along the skin texture and pat gently for better absorption. 1. After washing face or applying the pibubab gold grain pack in the evening and without applying the basic cosmetics, put a few of drops of energy ampule oil on your wet face, after while tap and rub lightly with your palm. 2. For the face, apply outwards and top-down for the neck. 3. It is also recommendable to apply after taking a shower.

DOSAGE & ADMINISTRATION

Dosage & Administration: Take an adequate amount of this product.